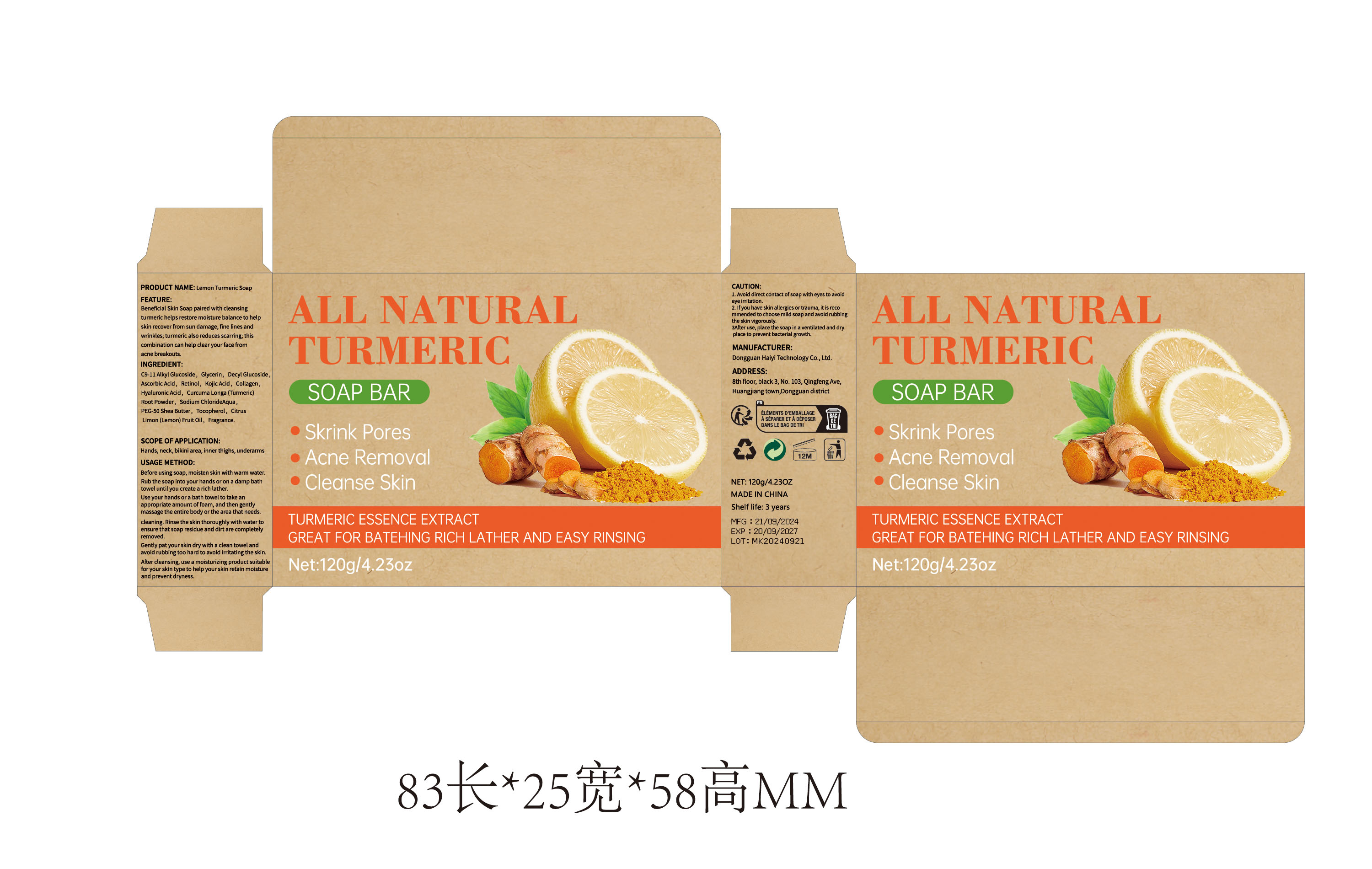 DRUG LABEL: Lemon Turmeric Bar
NDC: 84732-008 | Form: SOAP
Manufacturer: Dongguan Haiyi Technology Co.,Ltd.
Category: otc | Type: HUMAN OTC DRUG LABEL
Date: 20240924

ACTIVE INGREDIENTS: C9-11 ALKANE/CYCLOALKANE 1 g/120 g
INACTIVE INGREDIENTS: ASCORBIC ACID; PEG-50 SHEA BUTTER; TURMERIC; WATER; CITRUS LIMON FRUIT OIL; TOCOPHEROL; DECYL GLUCOSIDE; KOJIC ACID; EQUINE COLLAGEN; FRAGRANCE 13576; SODIUM CHLORIDE; GLYCERIN; HYALURONIC ACID

Active ingredient

C9-11 Alkyl Glucoside

INACTIVE INGREDIENT

Glycerin, Decyl Glucoside,Ascorbic Acid, Retinol, Kojic Acid, Collagen,Hyaluronic Acid, Curcuma Longa (Turmeric) Root Powder, Sodium Chloride，Aqua,PEG-50 Shea Butter, Tocopherol, Citrus Limon (Lemon) Fruit Oil, Fragrance.

Purpose section

Beneficial Skin Soap paired with cleansing turmeric helps restore moisture balance to help skin recover from sun damage, fine lines and wrinkles; turmeric also reduces scarring; this combination can help clear your face from acne breakouts

Warning

1. Avoid direct contact of soap with eyes to avoideye irritation.
2. lf you have skin allergies or trauma, it is recommended to choose mild soap and avoid rubbing the skin vigorously.

stop use

This product may cause allergic reactions in asmall number of people.
lf youexperience any discomfort,please stop using it immediately.

not use

Not suitable for use by children, pregnantor breast feeding people.

OUT OF CHILDREN

KEEP THE PRODUCT OUT OF REACH OF CHILDREN to

HOW TO USE

1.Before using soap, moisten skin with warm water.Rub the soap into your hands or on a damp bathtowel until you create a rich lather.

2.Use your hands or a bath towel to take anappropriate amount of foam, and then gentlymassage the entire body or the area that needs.
3.cleaning. Rinse the skin thoroughly with water toensure that soap residue and dirt are completelyremoved.
4.Gently pat your skin dry with a clean towel andavoid rubbing too hard to avoid irritating the skin.After cleansing, use a moisturizing 5.product suitablefor your skin type to help your skin retain moistureand prevent dryness.

Dosage

take an appropriateamount,Use 2-3 times a week